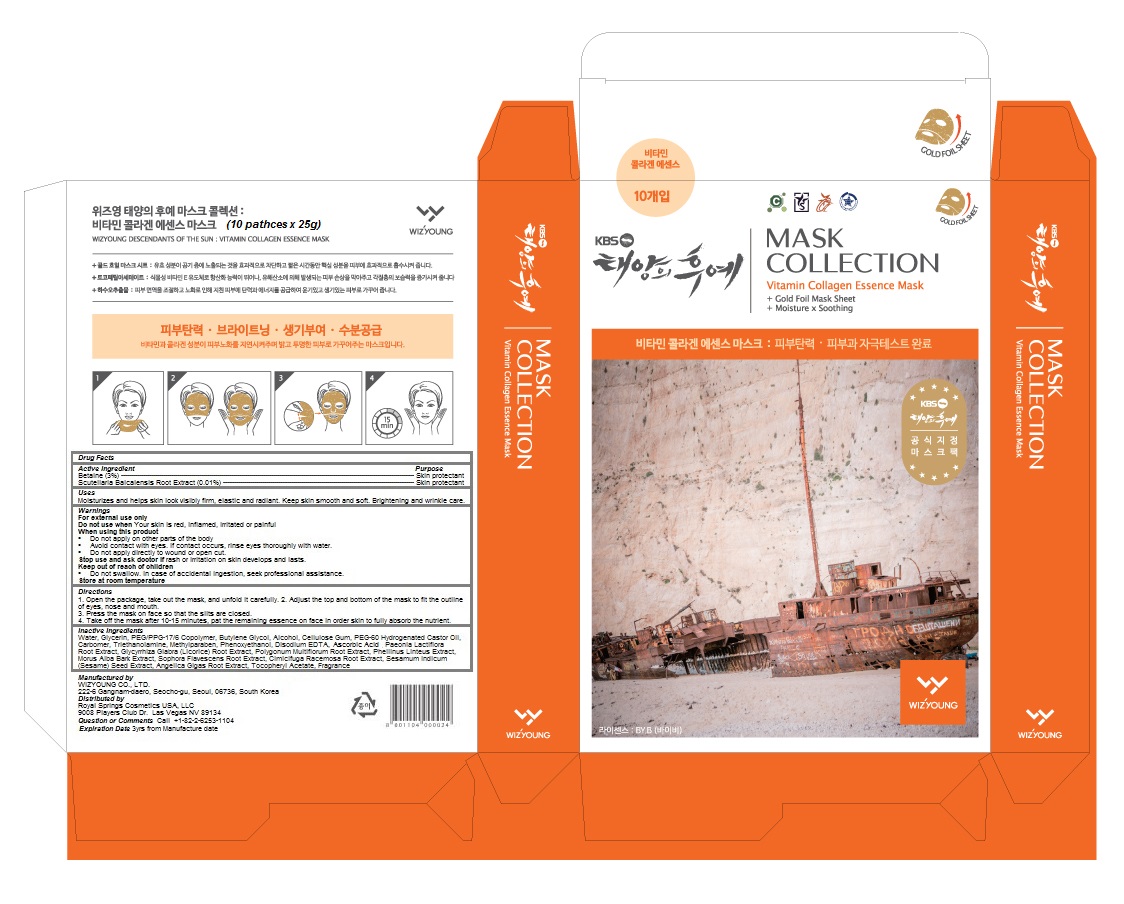 DRUG LABEL: Wizyoung Vitamin Collagen Essence Mask Pack
NDC: 71102-100 | Form: PATCH
Manufacturer: WIZYOUNG CO., LTD
Category: otc | Type: HUMAN OTC DRUG LABEL
Date: 20170301

ACTIVE INGREDIENTS: BETAINE 0.75 g/25 g; SCUTELLARIA BAICALENSIS ROOT 0.0025 g/25 g
INACTIVE INGREDIENTS: WATER; GLYCERIN; PEG/PPG-17/6 COPOLYMER; BUTYLENE GLYCOL; ALCOHOL; CARBOXYMETHYLCELLULOSE SODIUM, UNSPECIFIED FORM; PEG-60 HYDROGENATED CASTOR OIL; CARBOXYPOLYMETHYLENE; TROLAMINE; METHYLPARABEN; PHENOXYETHANOL; EDETATE DISODIUM ANHYDROUS; ASCORBIC ACID; PAEONIA LACTIFLORA ROOT; GLYCYRRHIZA GLABRA; FALLOPIA MULTIFLORA ROOT; MORUS ALBA BARK; SOPHORA FLAVESCENS ROOT; BLACK COHOSH; SESAME SEED; ANGELICA GIGAS ROOT; .ALPHA.-TOCOPHEROL ACETATE

Wizyoung Vitamin Collagen Essence Mask Pack

Active Ingredients

Betaine (3%)

Scutellaria Baicalensis Root Extract (0.01%)

Purpose

Skin protectant

Keep out of reach of children

 Do not swallow. In case of accidental ingestion, seek professional assistance.

Warnings

For external use only
Do not use when Your skin is red, inflamed, irritated or painful
When using this product
 Do not apply on other parts of the body
 Avoid contact with eyes. If contact occurs, rinse eyes thoroughly with water.
 Do not apply directly to wound or open cut.
Stop use and ask doctor if rash or irritation on skin develops and lasts.

Store at room temperature

Uses

Moisturizes and helps skin look visibly firm, elastic and radiant. Keep skin smooth and soft. Brightening and wrinkle care.

Directions

1. Open the package, take out the mask, and unfold it carefully.

2. Adjust the top and bottom of the mask to fit the outline of eyes, nose and mouth.

3. Press the mask on face so that the slits are closed.

4. Take off the mask after 10-15 minutes, pat the remaining essence on face in order skin to fully absorb the nutrient.

Inactive Ingredients

Water, Glycerin, PEG/PPG-17/6 Copolymer, Butylene Glycol, Alcohol, Cellulose Gum, PEG-60 Hydrogenated Castor Oil, Carbomer, Triethanolamine, Methylparaben, Phenoxyethanol, Disodium EDTA, Ascorbic Acid, Paeonia Lactiflora Root Extract, Glycyrrhiza Glabra (Licorice) Root Extract, Polygonum Multiflorum Root Extract, Phellinus Linteus Extract, Morus Alba Bark Extract, Sophora Flavescens Root Extract, Cimicifuga Racemosa Root Extract, Sesamum Indicum (Sesame) Seed Extract, Angelica Gigas Root Extract, Tocopheryl Acetate, Fragrance